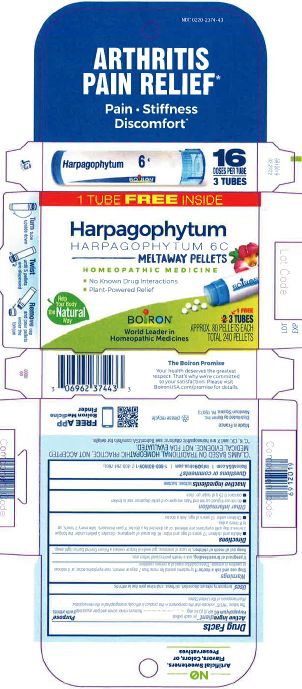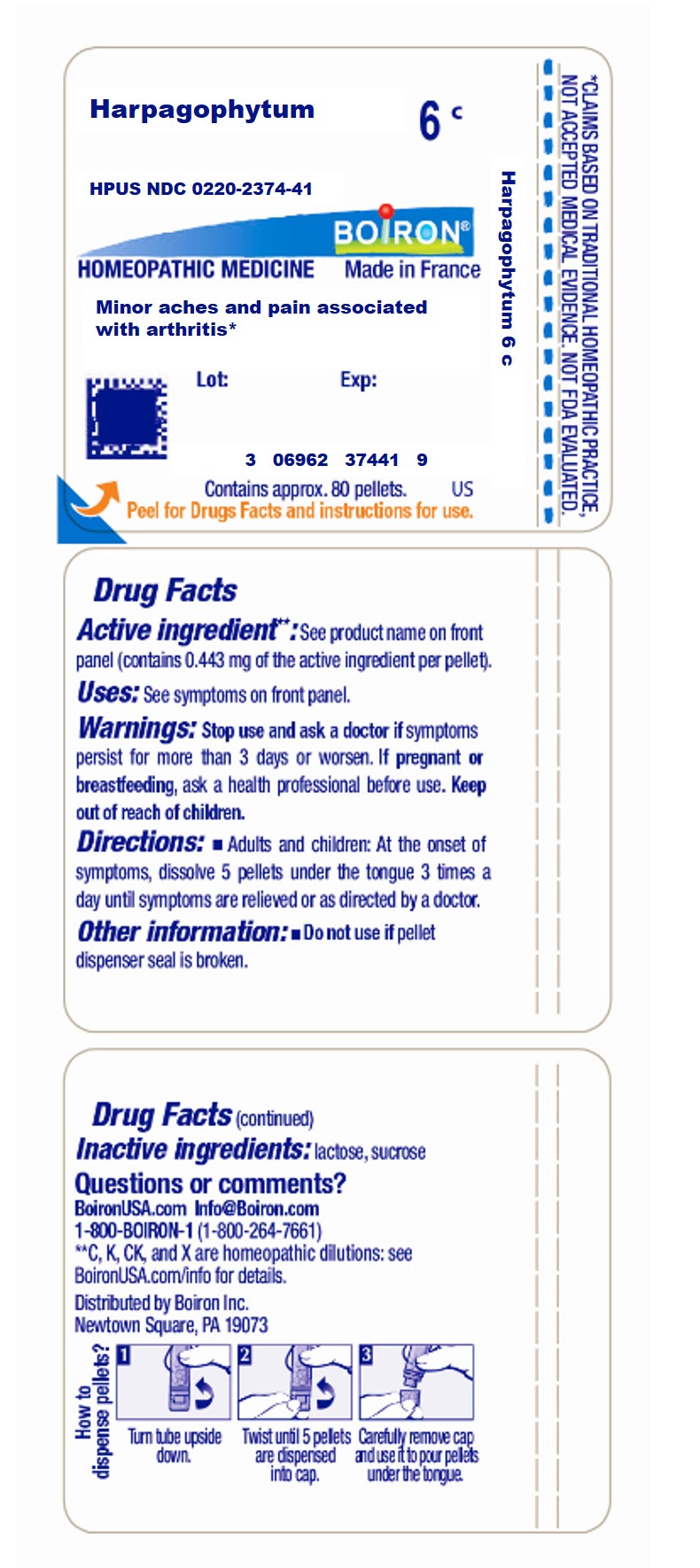 DRUG LABEL: HARPAGOPHYTUM
NDC: 0220-2374 | Form: PELLET
Manufacturer: Boiron
Category: homeopathic | Type: HUMAN OTC DRUG LABEL
Date: 20231221

ACTIVE INGREDIENTS: HARPAGOPHYTUM PROCUMBENS ROOT 6 [hp_C]/6 [hp_C]
INACTIVE INGREDIENTS: SUCROSE; LACTOSE, UNSPECIFIED FORM

HARPAGOPHYTUM 6C MD

Active Ingredient** (in each pellet)

Harpagophytum 6C HPUS (0.44 mg)

The letters "HPUS" indicate that the component in this product is officially monographed in the Homeopathic Pharmacopoeia of the United States.

Purpose*

Harpagophytum 6C HPUS (0.44 mg) ... Relieves minor aches and pain associated with arthritis

Uses*

Tube - Minor aches and pains associated with arthritis*

Box - temporarily relieves discomfort, stiffness, and minor pain due to arthritis

STOP USE

Tube - Stop use and ask a doctor if symptoms persist for more than 3 days or worsen

Box - Stop use and ask a doctor if symptoms persist for more than 7 days or worsen, new symptoms occur, or if redness or swelling is present. These could be signs of a serious condition.

PREGNANCY OR BREAST FEEDING

If pregnant or breast-feeding, ask a health professional before use.

Tube - Keep out of reach of children

Box - Keep out of reach of children. In case of overdoes, get medical help or contact a Poison Control Center right away.

Directions

Tube - Adults and children: At the onset of symptoms, dissolve 5 pellets under the tongue 3 times a day until symptoms are relieved or as directed by a doctor.

Box - Adults and children 12 years of age and older: At the onset of symptoms, dissolve 5 pellets under the tongue 3 times a day until symptoms are relieved, or as directed by a doctor. If pain increases, take every 2 hours, up to 8 times a day.

Children under 12 years of age: Ask a doctor

Tube - Do not use if pellet dispenser seal is broken.

Contains approx 80 pellets.

How to dispense pellets? Turn tube upside down. Twist until 5 pellets are dispensed into cap. Carefully remove the cap and use it to pour pellets under the tongue.

*CLAIMS BASED ON TRADITIONAL HOMEOPATHIC PRACTICE NOT ACCEPTED MEDICAL EVIDENCE. NOT FDA EVALUATED.
**C,K,CK, and X are homeopathic dilutions: see BoironUSA.com/info for details.

Box - do not use if glued carton end flaps are open or if the pellet dispenser seal is broken

contains 0.25 g of sugar per dose

Turn tube upside down Twist until 5 pellets are dispensed Remove cap and pour pellets under the tongue

Meltaway pellets

16 DOSES PER TUBE

3 TUBES

Approx. 80 pellets each

Total 240 pellets

Arthritis Pain Relief*

Pain Stiffness Discomfort*

*CLAIMS BASED ON TRADITIONAL HOMEOPATHIC PRACTICE NOT ACCEPTED MEDICAL EVIDENCE. NOT FDA EVALUATED.
**C,K,CK, and X are homeopathic dilutions: see BoironUSA.com/info for details.

INACTIVE INGREDIENT

lactose, sucrose

QUESTIONS

1-800-BOIRON-1 (1-800-264-7661),
BoironUSA.com Info@boiron.com

Made in France

Distributed by Boiron, Inc. Newtown Square, PA 19073